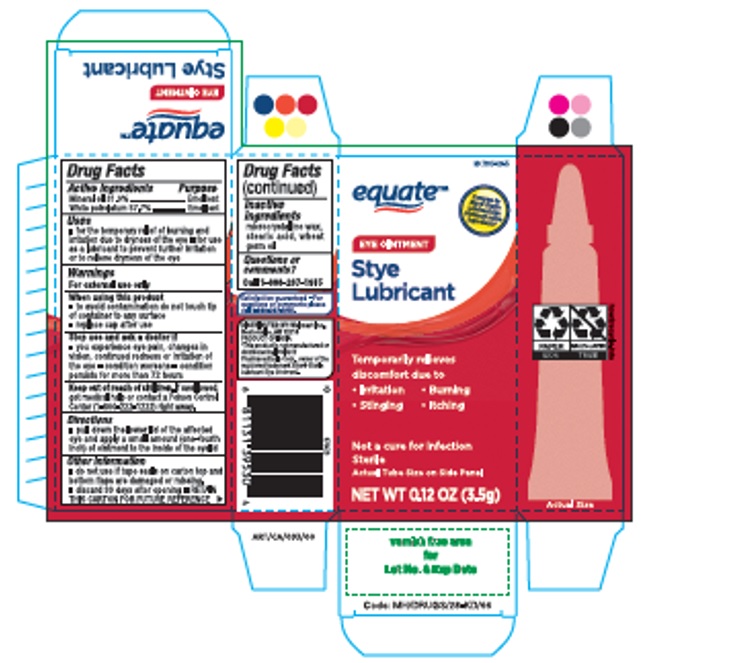 DRUG LABEL: EQUATE LUBRICANT EYE

NDC: 79903-028 | Form: OINTMENT
Manufacturer: WAL-MART STORES INC
Category: otc | Type: HUMAN OTC DRUG LABEL
Date: 20221120

ACTIVE INGREDIENTS: MINERAL OIL 319 mg/1 g; PETROLATUM 577 mg/1 g
INACTIVE INGREDIENTS: MICROCRYSTALLINE WAX; STEARIC ACID; WHEAT GERM OIL

Equate Stye Lubricant eye ointment

LUBRICANT EYE OINTMENT

Mineral oil 31.9%, White petrolatum 57.7%

Active ingredients

Mineral oil 31.9%

Purpose

Emollient

Active ingredients

White petrolatum 57.7%

Purpose

Emollient

Uses

- temporarily relieves burning and irritation of the eye and discomfort due to dryness of the eye or exposure to wind or sun
- as use as a protectant against further irritation

Warnings

For external use only

When using this product

- to avoid contamination do not touch tip of container to any surface
- replace cap after use

Stop use and ask a doctor if

- you experience eye pain, changes in vision, continued redness or irritation of the eye
- condition worsens
- condition persists for more than 72 hours

Keep out of reach of children.

If swallowed, get medical help or contact a Poison Control Center right away.

1-800-222-1222

Directions

- pull down the lower lid of the affected eye and apply a small amount (one-fourth inch) of ointment to the inside of the eyelid

Other information

discard 30 days after opening. Retain this carton for future reference.

Inactive Ingredients

microcrystalline wax, stearic acid, wheat germ oil